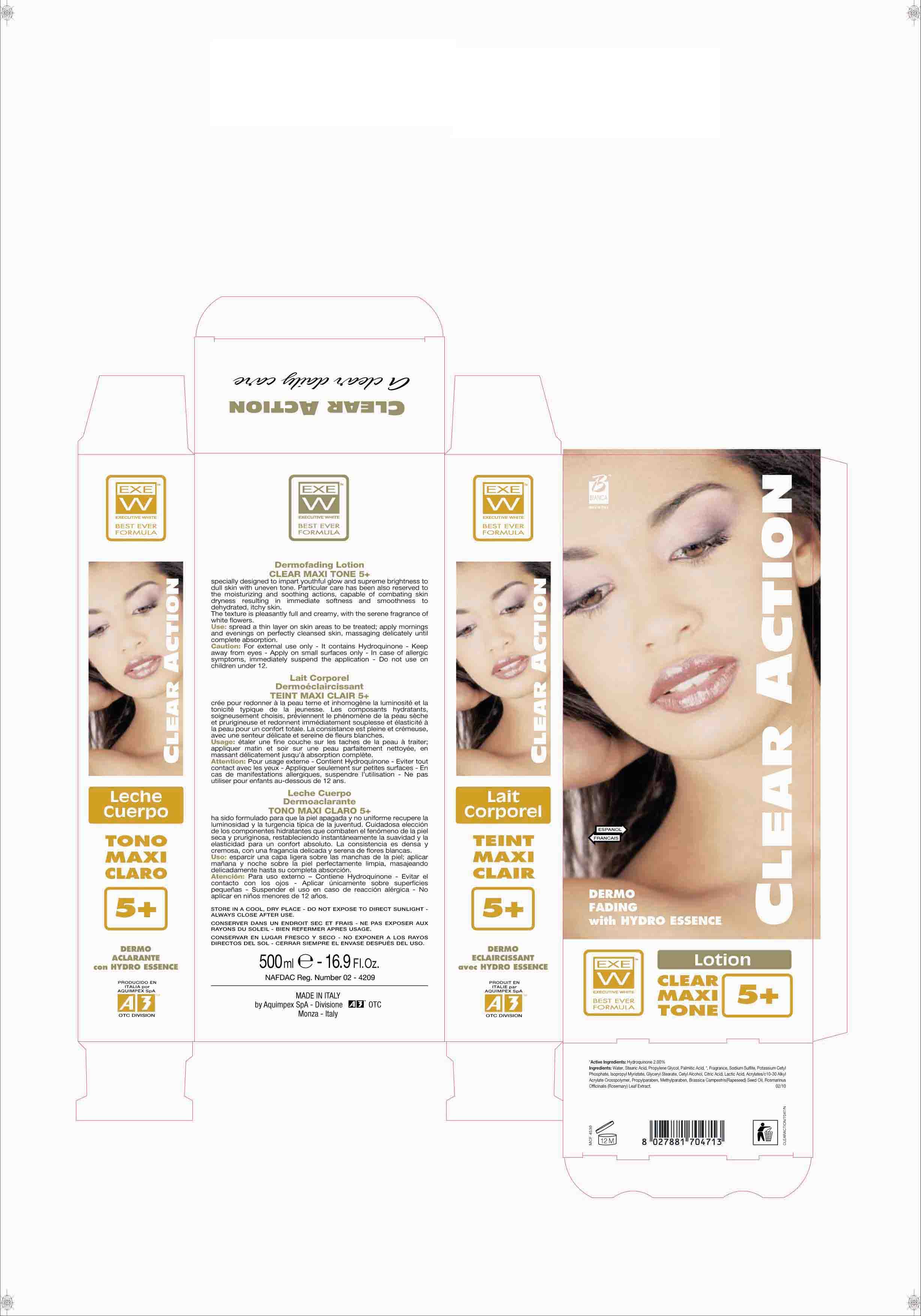 DRUG LABEL: CLEAR ACTION
NDC: 66273-0004 | Form: LOTION
Manufacturer: AQUIMPEX SPA
Category: otc | Type: HUMAN OTC DRUG LABEL
Date: 20110719

ACTIVE INGREDIENTS: HYDROQUINONE 10 mL/500 mL
INACTIVE INGREDIENTS: WATER; ROSEMARY; METHYLPARABEN; PROPYLENE GLYCOL; CARBOMER 934; CETYL ALCOHOL; STEARIC ACID; PALMITIC ACID; GLYCERYL MONOSTEARATE; ISOPROPYL MYRISTATE; POTASSIUM CETYL PHOSPHATE; PROPYLPARABEN; CITRIC ACID MONOHYDRATE; SODIUM SULFITE; BRASSICA RAPA VAR. RAPA OIL

Clear Action Dermofading Lotion Maxi Tone 5+

Dermofading Lotion - Lightening

Clear Action Dermofading Lotion CLEAR MAXI TONE 5+ specially designed to impart youthful glow and supreme brightness to dull skin with uneven tone.
The texture is pleasantly full and creamy, with the serene fragrance of white flowers.

Use

Use: spread a thin layer on skin areas to be treated; apply mornings and evenings on perfectly cleansed skin, massaging delicately until complete absorption.

Caution

Caution: For external use only - It contains Hydroquinone - Keep away from eyes - Apply on small surfaces only - In case of allergic symptoms, immediately suspend the application - Do not use on children under 12.

Active Ingredients

Active Ingredients: Hydroquinone 2.00%

Ingredients

Ingredients: Water, Stearic Acid, Propylene Glycol, Palmitic Acid, *, Fragrance, Sodium Sulfite, Potassium Cetyl Phosphate, Isopropyl Myristate, Glyceryl Stearate, Cetyl Alcohol, Citric Acid, Lactic Acid, Acrylates/c10-30 Alkyl Acrylate Crosspolymer, Propylparaben, Methylparaben, Brassica Campestris (Rapeseed) Seed Oil, Rosmarinus Officinalis (Rosemary) Leaf Extract.

STORAGE AND HANDLING

STORE IN A COOL, DRY PLACE - DO NOT EXPOSE TO DIRECT SUNLIGHT - ALWAYS CLOSE AFTER USE.

Use

Use: spread a thin layer on skin areas to be treated

Caution

Caution: For external use only - It contains Hydroquinone - Keep away from eyes - Apply on small surfaces only - In case of allergic symptoms, immediately suspend the application - Do not use on children under 12.